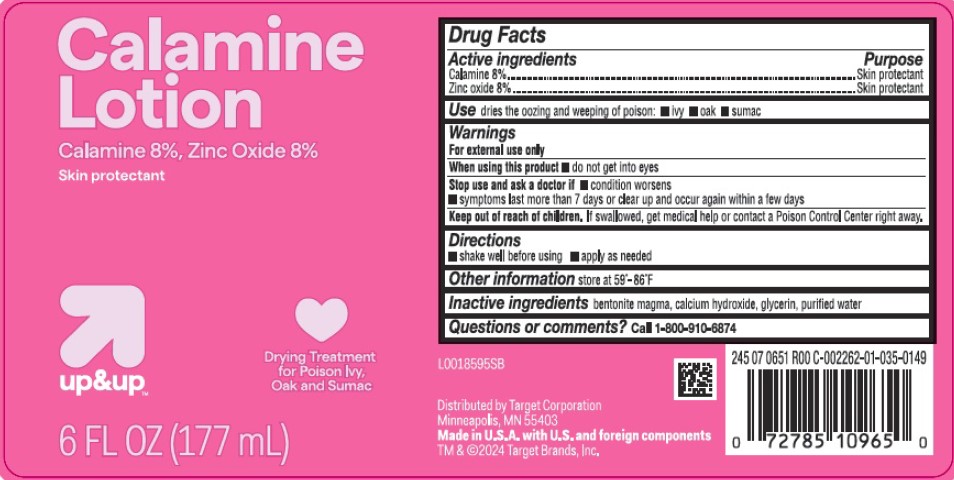 DRUG LABEL: Calamine
NDC: 11673-063 | Form: LOTION
Manufacturer: Target Corporation
Category: otc | Type: HUMAN OTC DRUG LABEL
Date: 20260218

ACTIVE INGREDIENTS: FERRIC OXIDE RED 80 mg/1 mL; ZINC OXIDE 80 mg/1 mL
INACTIVE INGREDIENTS: BENTONITE; CALCIUM HYDROXIDE; GLYCERIN; WATER

Up & Up 063.001/063AA
Calamine Lotion

Active ingredients

Calamine 8%

Zinc oxide 8%

Purpose

Skin protectant

Use

dries the oozing and weeping of poison:

- ivy
- oak
- sumac

Warnings

For external use only

When using this product

- do not get into eyes

Stop use and ask a doctor if

- condition worsens
- symptoms last more than 7 days or clear up and occur again within a few days

Keep out of reach of children.

If swallowed, get medical help or contact a Poison Control Center right away.

Directions

- shake well before using
- apply as needed

Other information

store at 59⁰-86⁰F

Inactive ingredients

bentonite magma, calcium hydroxide, glycerin, purified water

Questions or comments?

Call 1-800-910-6874

Adverse reaction

Distributed by Target Corporation

Minneapolis, MN 55403

Made in U.S.A. with U.S. and foreign components

TM & ©2024 Target Brands, Inc.

Principal display panel

Calamine

Lotion

Calamine 8%, Zinc Oxide 8

Skin Protectant

Drying Treatment for Poison Ivy, Oak and Sumac

up&up™

6 FL OZ (177 mL)